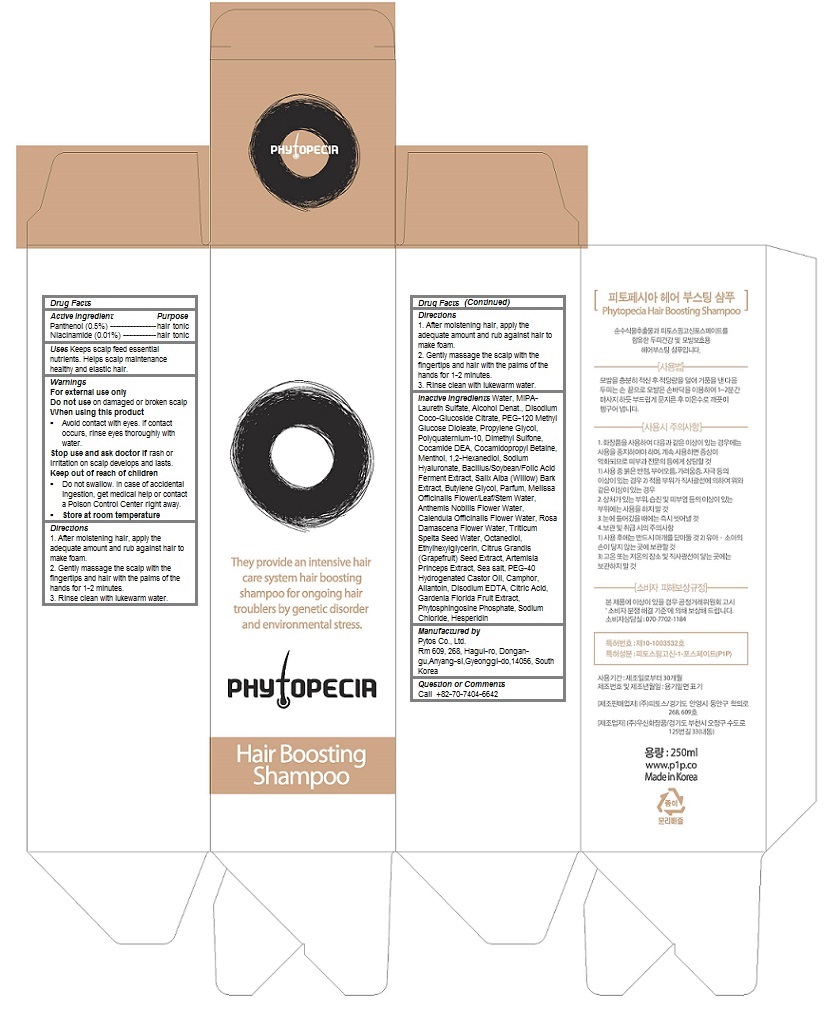 DRUG LABEL: Phytopecia Hair Boosting
NDC: 69579-107 | Form: SHAMPOO
Manufacturer: Phytos Co., Ltd.
Category: otc | Type: HUMAN OTC DRUG LABEL
Date: 20151218

ACTIVE INGREDIENTS: Panthenol 0.005 1/250 mL; Niacinamide 0.0001 1/250 mL
INACTIVE INGREDIENTS: WATER; ISOPROPANOLAMINE LAURYL SULFATE; ALCOHOL; PEG-120 METHYL GLUCOSE DIOLEATE; Propylene Glycol; Dimethyl Sulfone; COCO DIETHANOLAMIDE; COCAMIDOPROPYL BETAINE; MENTHOL; 1,2-Hexanediol; HYALURONATE SODIUM; SALIX ALBA BARK; Butylene Glycol; MELISSA OFFICINALIS FLOWERING TOP; CHAMAEMELUM NOBILE FLOWER OIL; CALENDULA OFFICINALIS FLOWER; ROSA DAMASCENA FLOWER OIL; Octanediol; Ethylhexylglycerin; CITRUS MAXIMA SEED; Sea salt; POLYOXYL 40 HYDROGENATED CASTOR oil; Allantoin; EDETATE DISODIUM; CITRIC ACID MONOHYDRATE; GARDENIA JASMINOIDES FRUIT; Sodium Chloride; Hesperidin

Phytopecia Hair Boosting Shampoo